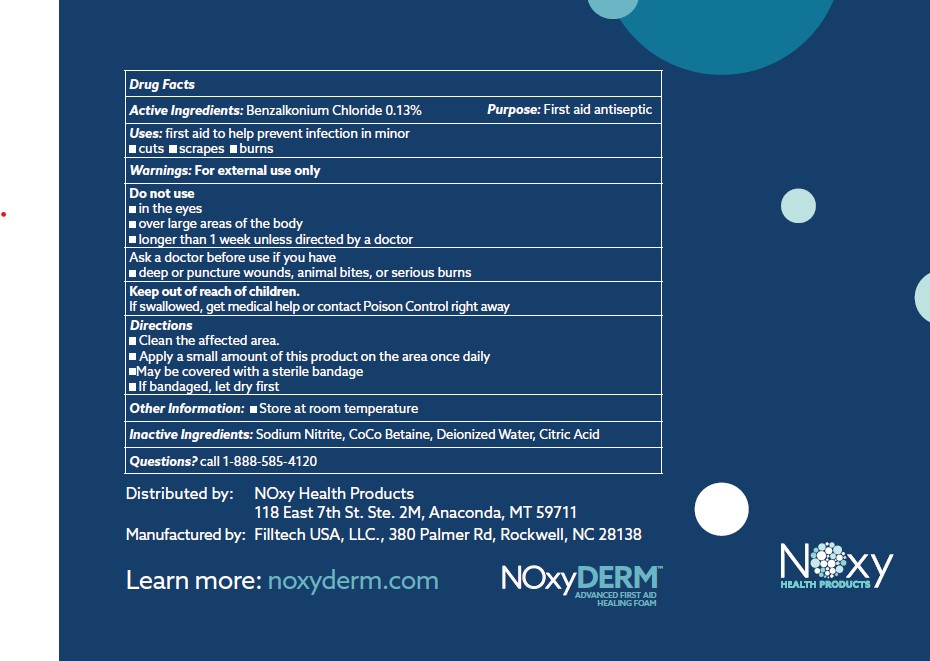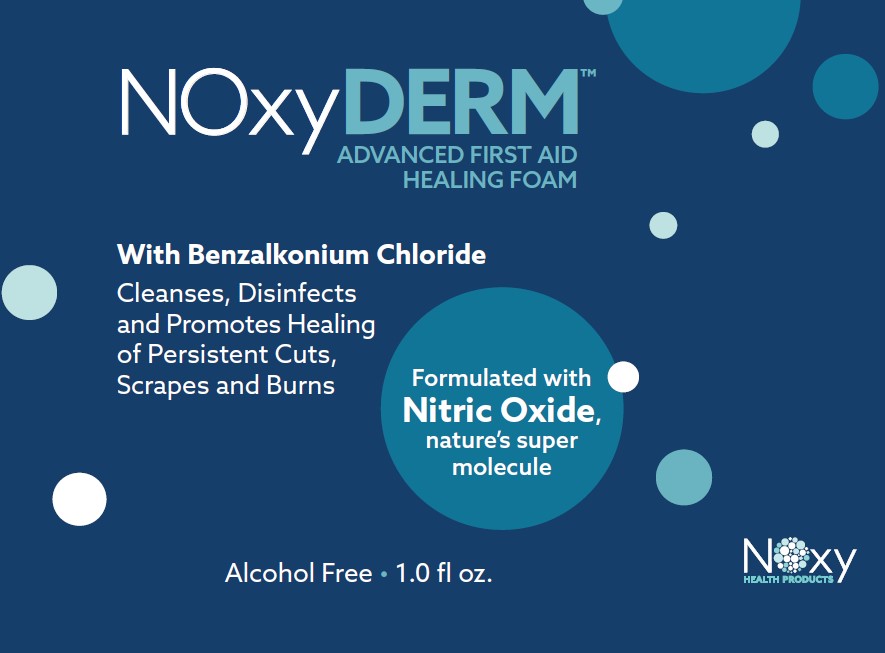 DRUG LABEL: NOxyDERM
NDC: 83823-002 | Form: LIQUID
Manufacturer: NOxy Health Products
Category: otc | Type: HUMAN OTC DRUG LABEL
Date: 20240726

ACTIVE INGREDIENTS: BENZALKONIUM CHLORIDE 0.038 g/29.5 mL
INACTIVE INGREDIENTS: SODIUM NITRITE; COCO-BETAINE; ANHYDROUS CITRIC ACID; WATER

Active Ingredient

Active Ingredient | Purpose
Benzalkonium Chloride 0.13% | First Aid Antiseptic

Purpose

First aid antiseptic

Uses: first aid to help prevent infection in minor:

- cuts
- scrapes
- burns

Do not use

- in the eyes
- over large areas of the body
- longer than 1 week unless directed by a doctor

Ask a doctor before use if you have

- deep or puncture wounds, animal bites, or serious burns

Warnings

For external use only

Keep out of reach of children. If swallowed, get medical help or contact Poison Control right away

Instructions for use

Directions

- Clean the affected area
- Apply a small amount of this product on the area once daily
- May be covered with a sterile bandage
- If bandaged, let dry first

Other safety information

Store at room temperature

Dosage

Apply a small amount of this product on the area once daily

Inactive ingredients

Sodium Nitrite

CoCo Betaine

Deionized Water

Citric Acid

Indications and usage

Directions:

- Clean the affected area
- Apply a small amount of this product on the area once daily
- May be covered with a sterile bandage
- If bandaged, let dry first

Warnings

Warnings: For external use only

Questions

Questions? call 1-888-585-4120